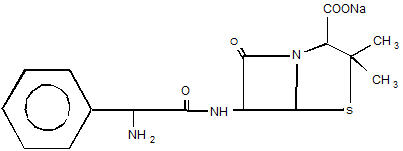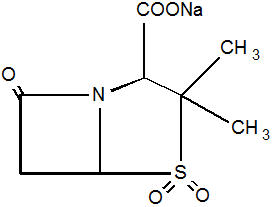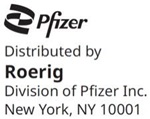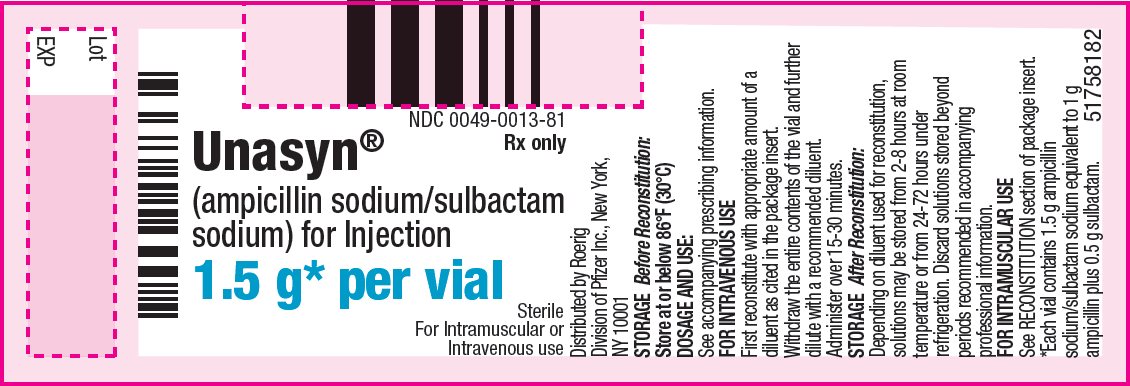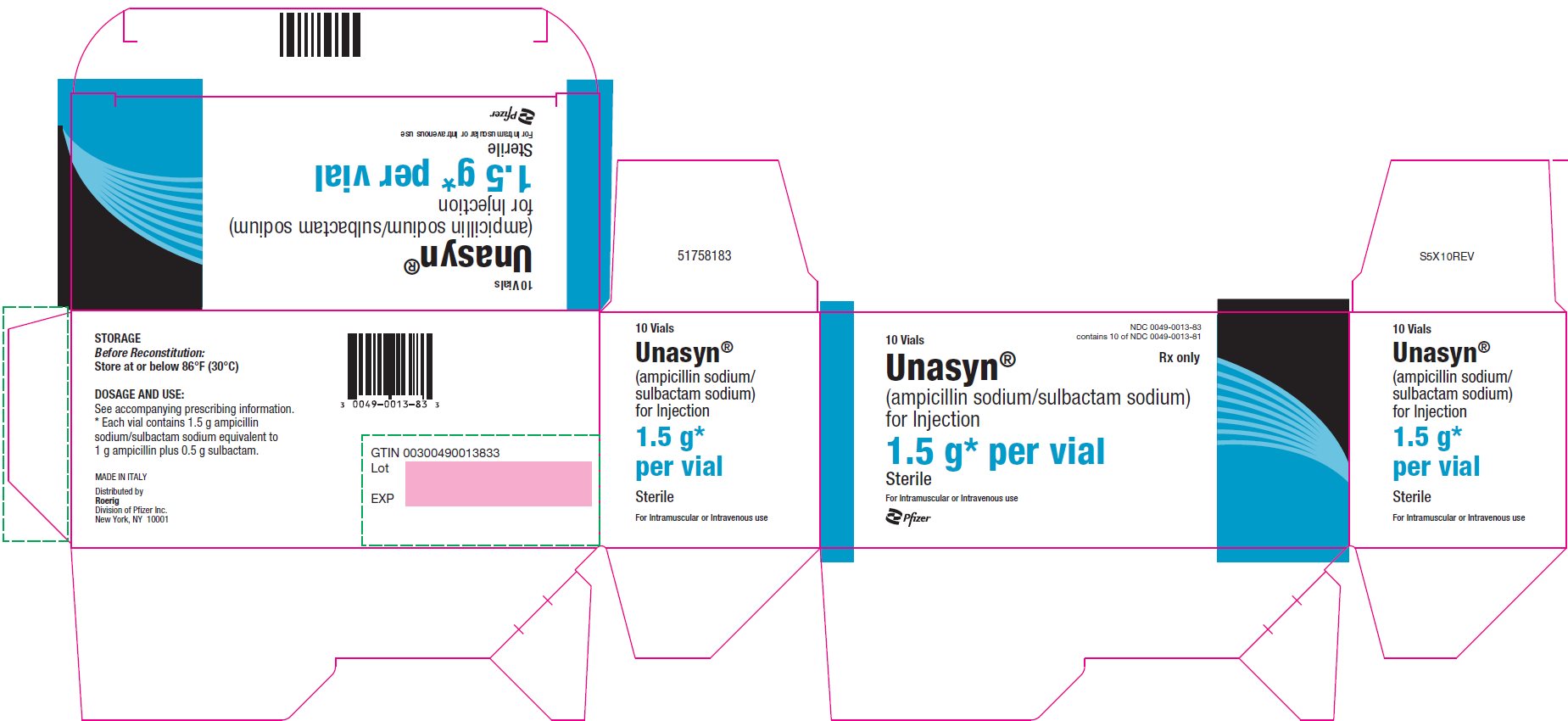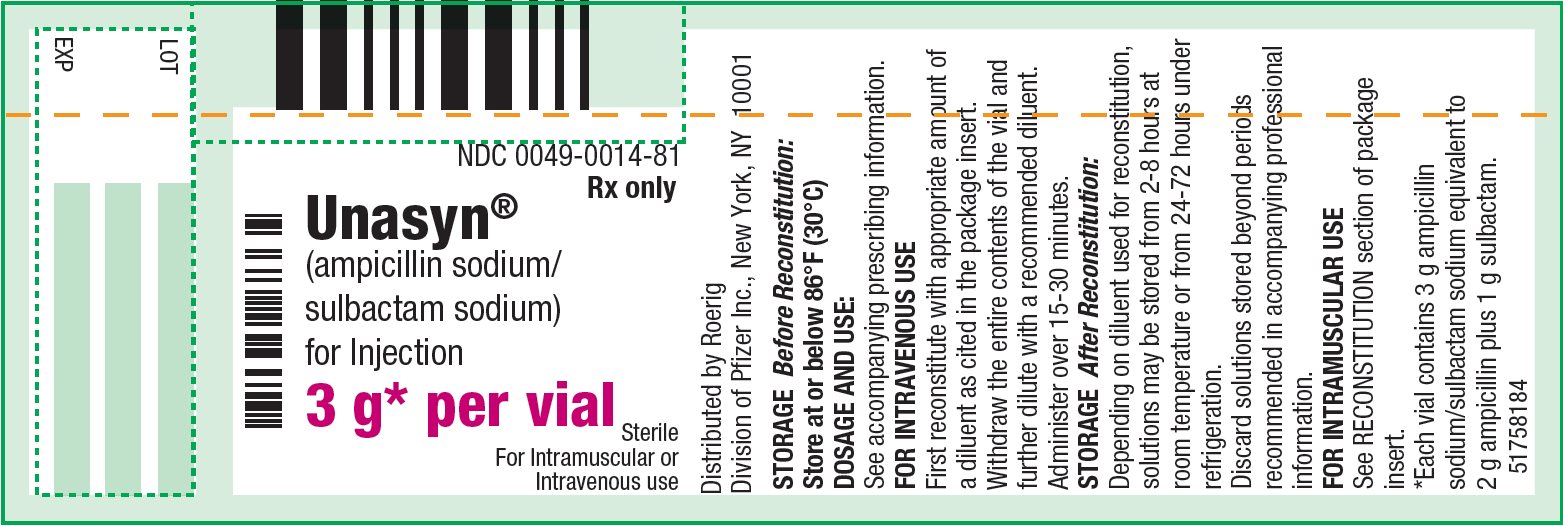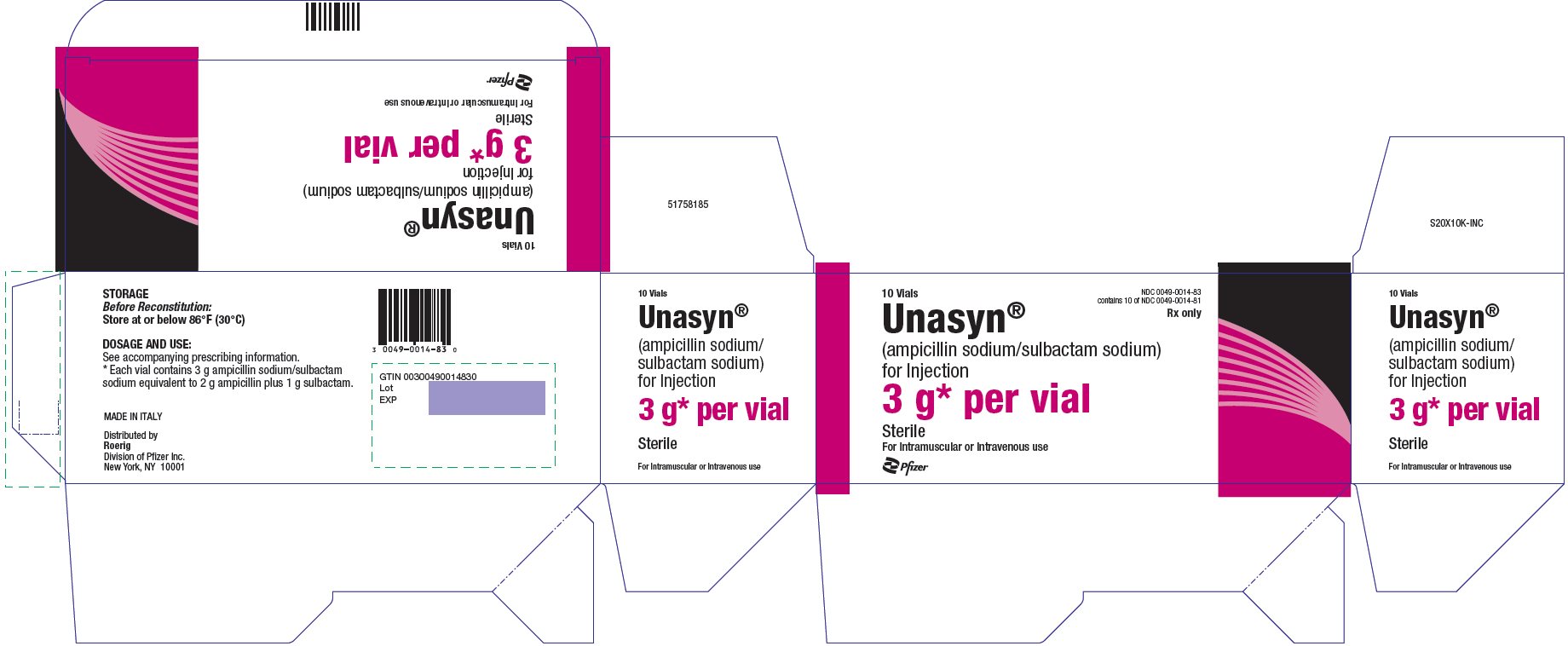 DRUG LABEL: UNASYN
NDC: 0049-0013 | Form: INJECTION, POWDER, FOR SOLUTION
Manufacturer: Roerig
Category: prescription | Type: HUMAN PRESCRIPTION DRUG LABEL
Date: 20250514

ACTIVE INGREDIENTS: AMPICILLIN SODIUM 1 g/1 1; SULBACTAM SODIUM 0.5 g/1 1

UNASYN®
(ampicillin sodium and sulbactam sodium)
For Injection, USP

To reduce the development of drug-resistant bacteria and maintain the effectiveness of UNASYN® and other antibacterial drugs, UNASYN should be used only to treat infections that are proven or strongly suspected to be caused by bacteria.

DESCRIPTION

UNASYN (ampicillin sodium and sulbactam sodium) for Injection, USP is an injectable antibacterial combination consisting of the semisynthetic antibacterial ampicillin sodium and the beta-lactamase inhibitor sulbactam sodium for intravenous and intramuscular administration.

Ampicillin sodium is derived from the penicillin nucleus, 6-aminopenicillanic acid. Chemically, it is monosodium (2S, 5R, 6R)-6-[(R)-2-amino-2-phenylacetamido]-3,3-dimethyl-7-oxo-4-thia-1-azabicyclo[3.2.0]heptane-2-carboxylate and has a molecular weight of 371.39. Its chemical formula is C16H18N3NaO4S. The structural formula is:

Sulbactam sodium is a derivative of the basic penicillin nucleus. Chemically, sulbactam sodium is sodium penicillinate sulfone; sodium (2S, 5R)-3,3-dimethyl-7-oxo-4-thia- 1-azabicyclo [3.2.0] heptane-2-carboxylate 4,4-dioxide. Its chemical formula is C8H10NNaO5S with a molecular weight of 255.22. The structural formula is:

UNASYN, ampicillin sodium and sulbactam sodium parenteral combination, is available as a white to off-white dry powder for reconstitution. UNASYN dry powder is freely soluble in aqueous diluents to yield pale yellow to yellow solutions containing ampicillin sodium and sulbactam sodium equivalent to 250 mg ampicillin per mL and 125 mg sulbactam per mL. The pH of the solutions is between 8.0 and 10.0.

Dilute solutions (up to 30 mg ampicillin and 15 mg sulbactam per mL) are essentially colorless to pale yellow. The pH of dilute solutions remains the same.

1.5 g of UNASYN (1 g ampicillin as the sodium salt plus 0.5 g sulbactam as the sodium salt) parenteral contains approximately 115 mg (5 mEq) of sodium.

3 g of UNASYN (2 g ampicillin as the sodium salt plus 1 g sulbactam as the sodium salt) parenteral contains approximately 230 mg (10 mEq) of sodium.

CLINICAL PHARMACOLOGY

General

Immediately after completion of a 15-minute intravenous infusion of UNASYN, peak serum concentrations of ampicillin and sulbactam are attained. Ampicillin serum levels are similar to those produced by the administration of equivalent amounts of ampicillin alone. Peak ampicillin serum levels ranging from 109 to 150 mcg/mL are attained after administration of 2000 mg of ampicillin plus 1000 mg sulbactam and 40 to 71 mcg/mL after administration of 1000 mg ampicillin plus 500 mg sulbactam. The corresponding mean peak serum levels for sulbactam range from 48 to 88 mcg/mL and 21 to 40 mcg/mL, respectively. After an intramuscular injection of 1000 mg ampicillin plus 500 mg sulbactam, peak ampicillin serum levels ranging from 8 to 37 mcg/mL and peak sulbactam serum levels ranging from 6 to 24 mcg/mL are attained.

The mean serum half-life of both drugs is approximately 1 hour in healthy volunteers.

Approximately 75 to 85% of both ampicillin and sulbactam are excreted unchanged in the urine during the first 8 hours after administration of UNASYN to individuals with normal renal function. Somewhat higher and more prolonged serum levels of ampicillin and sulbactam can be achieved with the concurrent administration of probenecid.

In patients with impaired renal function the elimination kinetics of ampicillin and sulbactam are similarly affected, hence the ratio of one to the other will remain constant whatever the renal function. The dose of UNASYN in such patients should be administered less frequently in accordance with the usual practice for ampicillin (see DOSAGE AND ADMINISTRATION section).

Ampicillin has been found to be approximately 28% reversibly bound to human serum protein and sulbactam approximately 38% reversibly bound.

The following average levels of ampicillin and sulbactam were measured in the tissues and fluids listed:

TABLE 1 Concentration of UNASYN in Various Body Tissues and Fluids
Fluid or Tissue | Dose (grams) Ampicillin/Sulbactam | Concentration (mcg/mL or mcg/g) Ampicillin/Sulbactam
Peritoneal Fluid | 0.5/0.5 IV | 7/14
Blister Fluid (Cantharides) | 0.5/0.5 IV | 8/20
Tissue Fluid | 1/0.5 IV | 8/4
Intestinal Mucosa | 0.5/0.5 IV | 11/18
Appendix | 2/1 IV | 3/40

Penetration of both ampicillin and sulbactam into cerebrospinal fluid in the presence of inflamed meninges has been demonstrated after IV administration of UNASYN.

The pharmacokinetics of ampicillin and sulbactam in pediatric patients receiving UNASYN are similar to those observed in adults. Immediately after a 15-minute infusion of 50 to 75 mg UNASYN/kg body weight, peak serum and plasma concentrations of 82 to 446 mcg ampicillin/mL and 44 to 203 mcg sulbactam/mL were obtained. Mean half-life values were approximately 1 hour.

MICROBIOLOGY

Mechanism of Action

Ampicillin is similar to benzyl penicillin in its bactericidal action against susceptible organisms during the stage of active multiplication. It acts through the inhibition of cell wall mucopeptide biosynthesis. Ampicillin has a broad spectrum of bactericidal activity against many gram-positive and gram-negative aerobic and anaerobic bacteria. (Ampicillin is, however, degraded by beta-lactamases and therefore the spectrum of activity does not normally include organisms which produce these enzymes).

A wide range of beta-lactamases found in microorganisms resistant to penicillins and cephalosporins have been shown in biochemical studies with cell free bacterial systems to be irreversibly inhibited by sulbactam. Although sulbactam alone possesses little useful antibacterial activity except against the Neisseriaceae, whole organism studies have shown that sulbactam restores ampicillin activity against beta-lactamase producing strains. In particular, sulbactam has good inhibitory activity against the clinically important plasmid mediated beta-lactamases most frequently responsible for transferred drug resistance. Sulbactam has no effect on the activity of ampicillin against ampicillin-susceptible strains.

The presence of sulbactam in the UNASYN formulation effectively extends the antibacterial spectrum of ampicillin to include many bacteria normally resistant to it and to other beta-lactam antibacterials. Thus, UNASYN possesses the properties of a broad-spectrum antibacterial and a beta-lactamase inhibitor.

Antimicrobial Activity

While in vitro studies have demonstrated the susceptibility of most strains of the following organisms, clinical efficacy for infections other than those included in the INDICATIONS AND USAGE section has not been documented.

Gram-positive Bacteria:

Staphylococcus aureus (beta-lactamase and non-beta-lactamase producing)

Staphylococcus epidermidis (beta-lactamase and non-beta-lactamase producing)

Staphylococcus saprophyticus (beta-lactamase and non-beta-lactamase producing)

Enterococcus faecalis

Streptococcus pneumoniae

Streptococcus pyogenes

Streptococcus viridans

Gram-negative Bacteria:

Hemophilus influenzae (beta-lactamase and non-beta-lactamase producing)

Moraxella catarrhalis (beta-lactamase and non-beta-lactamase producing)

Escherichia coli (beta-lactamase and non-beta-lactamase producing)

Klebsiella species (all known strains are beta-lactamase producing)

Proteus mirabilis (beta-lactamase and non-beta-lactamase producing)

Proteus vulgaris

Providencia rettgeri

Providencia stuartii

Morganella morganii

Neisseria gonorrhoeae (beta-lactamase and non-beta-lactamase producing)

Anaerobes:

Clostridium species [These are not beta-lactamase producing strains and, therefore, are susceptible to ampicillin alone.]

Peptococcus species

Peptostreptococcus species

Bacteroides species, including B. fragilis

Susceptibility Testing

For specific information regarding susceptibility test interpretive criteria and associated test methods and quality control standards recognized by FDA for this drug, please see: https://www.fda.gov/STIC.

INDICATIONS AND USAGE

UNASYN is indicated for the treatment of infections due to susceptible strains of the designated microorganisms in the conditions listed below.

Skin and Skin Structure Infections caused by beta-lactamase producing strains of Staphylococcus aureus, Escherichia coli, [Efficacy for this organism in this organ system was studied in fewer than 10 infections.] Klebsiella spp. (including K. pneumoniae), Proteus mirabilis, Bacteroides fragilis, Enterobacter spp., and Acinetobacter calcoaceticus.

NOTE: For information on use in pediatric patients (see PRECAUTIONS–Pediatric Use and CLINICAL STUDIES sections).

Intra-Abdominal Infections caused by beta-lactamase producing strains of Escherichia coli, Klebsiella spp. (including K. pneumoniae), Bacteroides spp. (including B. fragilis), and Enterobacter spp.

Gynecological Infections caused by beta-lactamase producing strains of Escherichia coli, and Bacteroides spp. (including B. fragilis).

While UNASYN is indicated only for the conditions listed above, infections caused by ampicillin-susceptible organisms are also amenable to treatment with UNASYN due to its ampicillin content. Therefore, mixed infections caused by ampicillin-susceptible organisms and beta-lactamase producing organisms susceptible to UNASYN should not require the addition of another antibacterial.

Appropriate culture and susceptibility tests should be performed before treatment in order to isolate and identify the organisms causing infection and to determine their susceptibility to UNASYN.

Therapy may be instituted prior to obtaining the results from bacteriological and susceptibility studies when there is reason to believe the infection may involve any of the beta-lactamase producing organisms listed above in the indicated organ systems. Once the results are known, therapy should be adjusted if appropriate.

To reduce the development of drug-resistant bacteria and maintain effectiveness of UNASYN and other antibacterial drugs, UNASYN should be used only to treat infections that are proven or strongly suspected to be caused by susceptible bacteria. When culture and susceptibility information are available, they should be considered in selecting or modifying antibacterial therapy. In the absence of such data, local epidemiology and susceptibility patterns may contribute to the empiric selection of therapy.

CONTRAINDICATIONS

The use of UNASYN is contraindicated in individuals with a history of serious hypersensitivity reactions (e.g., anaphylaxis or Stevens-Johnson syndrome) to ampicillin, sulbactam or to other beta-lactam antibacterial drugs (e.g., penicillins and cephalosporins).

UNASYN is contraindicated in patients with a previous history of cholestatic jaundice/hepatic dysfunction associated with UNASYN.

WARNINGS

Hypersensitivity

Serious and occasionally fatal hypersensitivity (anaphylactic) reactions have been reported in patients on penicillin therapy. These reactions are more apt to occur in individuals with a history of penicillin hypersensitivity and/or hypersensitivity reactions to multiple allergens. There have been reports of individuals with a history of penicillin hypersensitivity who have experienced severe reactions when treated with cephalosporins. Before therapy with a penicillin, careful inquiry should be made concerning previous hypersensitivity reactions to penicillins, cephalosporins, and other allergens. If an allergic reaction occurs, UNASYN should be discontinued and the appropriate therapy instituted.

Hepatotoxicity

Hepatic dysfunction, including hepatitis and cholestatic jaundice has been associated with the use of UNASYN. Hepatic toxicity is usually reversible; however, deaths have been reported. Hepatic function should be monitored at regular intervals in patients with hepatic impairment.

Severe Cutaneous Adverse Reactions

UNASYN may cause severe skin reactions, such as toxic epidermal necrolysis (TEN), Stevens-Johnson syndrome (SJS), drug reaction with eosinophilia and systemic symptoms (DRESS), dermatitis exfoliative, erythema multiforme, and Acute generalized exanthematous pustulosis (AGEP). If patients develop a skin rash they should be monitored closely and UNASYN discontinued if lesions progress (see CONTRAINDICATIONS and ADVERSE REACTIONS sections).

Clostridioides difficile-associated diarrhea (CDAD) has been reported with use of nearly all antibacterial agents, including UNASYN, and may range in severity from mild diarrhea to fatal colitis. Treatment with antibacterial agents alters the normal flora of the colon leading to overgrowth of C. difficile.

C. difficile produces toxins A and B which contribute to the development of CDAD. Hypertoxin producing strains of C. difficile cause increased morbidity and mortality, as these infections can be refractory to antimicrobial therapy and may require colectomy. CDAD must be considered in all patients who present with diarrhea following antibacterial drug use. Careful medical history is necessary since CDAD has been reported to occur over two months after the administration of antibacterial agents.

If CDAD is suspected or confirmed, ongoing antibacterial drug use not directed against C. difficile may need to be discontinued. Appropriate fluid and electrolyte management, protein supplementation, antibacterial treatment of C. difficile, and surgical evaluation should be instituted as clinically indicated.

PRECAUTIONS

General

A high percentage of patients with mononucleosis who receive ampicillin develop a skin rash. Thus, ampicillin class antibacterials should not be administered to patients with mononucleosis. In patients treated with UNASYN the possibility of superinfections with mycotic or bacterial pathogens should be kept in mind during therapy. If superinfections occur (usually involving Pseudomonas or Candida), the drug should be discontinued and/or appropriate therapy instituted.

Prescribing UNASYN in the absence of proven or strongly suspected bacterial infection or a prophylactic indication is unlikely to provide benefit to the patient and increases the risk of the development of drug-resistant bacteria.

Information for Patients

Patients should be counseled that antibacterial drugs including UNASYN should only be used to treat bacterial infections. They do not treat viral infections (e.g., the common cold). When UNASYN is prescribed to treat a bacterial infection, patients should be told that although it is common to feel better early in the course of therapy, the medication should be taken exactly as directed. Skipping doses or not completing the full course of therapy may (1) decrease the effectiveness of the immediate treatment and (2) increase the likelihood that bacteria will develop resistance and will not be treatable by UNASYN or other antibacterial drugs in the future.

Diarrhea is a common problem caused by antibacterials which usually ends when the antibacterial is discontinued. Sometimes after starting treatment with antibacterials, patients can develop watery and bloody stools (with or without stomach cramps and fever) even as late as two or more months after having taken the last dose of the antibacterial. If this occurs, patients should contact their physician as soon as possible.

Drug Interactions

Probenecid decreases the renal tubular secretion of ampicillin and sulbactam. Concurrent use of probenecid with UNASYN may result in increased and prolonged blood levels of ampicillin and sulbactam. The concurrent administration of allopurinol and ampicillin increases substantially the incidence of rashes in patients receiving both drugs as compared to patients receiving ampicillin alone. It is not known whether this potentiation of ampicillin rashes is due to allopurinol or the hyperuricemia present in these patients. There are no data with UNASYN and allopurinol administered concurrently. UNASYN and aminoglycosides should not be reconstituted together due to the in vitro inactivation of aminoglycosides by the ampicillin component of UNASYN.

Drug/Laboratory Test Interactions

Administration of UNASYN will result in high urine concentration of ampicillin. High urine concentrations of ampicillin may result in false positive reactions when testing for the presence of glucose in urine using Clinitest™, Benedict's Solution or Fehling's Solution. It is recommended that glucose tests based on enzymatic glucose oxidase reactions (such as Clinistix™ or Testape™) be used. Following administration of ampicillin to pregnant women, a transient decrease in plasma concentration of total conjugated estriol, estriol-glucuronide, conjugated estrone and estradiol has been noted. This effect may also occur with UNASYN.

Carcinogenesis, Mutagenesis, Impairment of Fertility

Long-term studies in animals have not been performed to evaluate carcinogenic or mutagenic potential.

Pregnancy

Reproduction studies have been performed in mice, rats, and rabbits at doses up to ten (10) times the human dose and have revealed no evidence of impaired fertility or harm to the fetus due to UNASYN. There are, however, no adequate and well-controlled studies in pregnant women. Because animal reproduction studies are not always predictive of human response, this drug should be used during pregnancy only if clearly needed. (see PRECAUTIONS-Drug/Laboratory Test Interactions section).

Labor and Delivery

Studies in guinea pigs have shown that intravenous administration of ampicillin decreased the uterine tone, frequency of contractions, height of contractions, and duration of contractions. However, it is not known whether the use of UNASYN in humans during labor or delivery has immediate or delayed adverse effects on the fetus, prolongs the duration of labor, or increases the likelihood that forceps delivery or other obstetrical intervention or resuscitation of the newborn will be necessary.

Nursing Mothers

Low concentrations of ampicillin and sulbactam are excreted in the milk; therefore, caution should be exercised when UNASYN is administered to a nursing woman.

Pediatric Use

The safety and effectiveness of UNASYN have been established for pediatric patients one year of age and older for skin and skin structure infections as approved in adults. Use of UNASYN in pediatric patients is supported by evidence from adequate and well-controlled studies in adults with additional data from pediatric pharmacokinetic studies, a controlled clinical trial conducted in pediatric patients and post-marketing adverse events surveillance. (see CLINICAL PHARMACOLOGY, INDICATIONS AND USAGE, ADVERSE REACTIONS, DOSAGE AND ADMINISTRATION, and CLINICAL STUDIES sections).

The safety and effectiveness of UNASYN have not been established for pediatric patients for intra-abdominal infections.

ADVERSE REACTIONS

Adult Patients

UNASYN is generally well tolerated. The following adverse reactions have been reported in clinical trials.

Local Adverse Reactions

Pain at IM injection site – 16%
Pain at IV injection site – 3%
Thrombophlebitis – 3%
Phlebitis – 1.2%

Systemic Adverse Reactions

The most frequently reported adverse reactions were diarrhea in 3% of the patients and rash in less than 2% of the patients.

Additional systemic reactions reported in less than 1% of the patients were: itching, nausea, vomiting, candidiasis, fatigue, malaise, headache, chest pain, flatulence, abdominal distension, glossitis, urine retention, dysuria, edema, facial swelling, erythema, chills, tightness in throat, substernal pain, epistaxis and mucosal bleeding.

Pediatric Patients

Available safety data for pediatric patients treated with UNASYN demonstrate a similar adverse events profile to those observed in adult patients. Additionally, atypical lymphocytosis has been observed in one pediatric patient receiving UNASYN.

Adverse laboratory changes without regard to drug relationship that were reported during clinical trials were:

Hepatic: Increased AST (SGOT), ALT (SGPT), alkaline phosphatase, and LDH.
Hematologic: Decreased hemoglobin, hematocrit, RBC, WBC, neutrophils, lymphocytes, platelets and increased lymphocytes, monocytes, basophils, eosinophils, and platelets.
Blood Chemistry: Decreased serum albumin and total proteins.
Renal: Increased BUN and creatinine.
Urinalysis: Presence of RBC's and hyaline casts in urine.

Post-marketing Experience

In addition to adverse reactions reported from clinical trials, the following have been identified during post-marketing use of ampicillin sodium and sulbactam sodium or other products containing ampicillin. Because they are reported voluntarily from a population of unknown size, estimates of frequency cannot be made. These events have been chosen for inclusion due to a combination of their seriousness, frequency, or potential causal connection to ampicillin sodium and sulbactam sodium.

Infections and Infestations: Clostridioides difficile-associated diarrhea (see WARNINGS section).

Blood and Lymphatic System Disorders: Hemolytic anemia, thrombocytopenic purpura, and agranulocytosis have been reported. These reactions are usually reversible on discontinuation of therapy and are believed to be hypersensitivity phenomena. Some individuals have developed positive direct Coombs Tests during treatment with UNASYN, as with other beta-lactam antibacterials.

Gastrointestinal Disorders: Abdominal pain, cholestatic hepatitis, cholestasis, hyperbilirubinemia, jaundice, abnormal hepatic function, melena, gastritis, stomatitis, dyspepsia, and black "hairy" tongue (see CONTRAINDICATIONS and WARNINGS sections).

General Disorders and Administration Site Conditions: Injection site reaction

Immune System Disorders: Serious and fatal hypersensitivity (anaphylactic) reactions (see WARNINGS section), Acute myocardial ischemia with or without myocardial infarction may occur as part of an allergic reaction.

Metabolism and Nutrition Disorders: Hypokalemia

Nervous System Disorders: Convulsion and dizziness

Renal and Urinary Disorders: Tubulointerstitial nephritis

Musculoskeletal and Connective Tissue Disorders: Arthralgia

Respiratory, Thoracic and Mediastinal Disorders: Dyspnea

Skin and Subcutaneous Tissue Disorders: Toxic epidermal necrolysis, Stevens-Johnson syndrome, drug reaction with eosinophilia and systemic symptoms (DRESS), angioedema, Acute generalized exanthematous pustulosis (AGEP), erythema multiforme, exfoliative dermatitis, urticaria (see CONTRAINDICATIONS and WARNINGS sections), and linear IgA bullous dermatosis.

OVERDOSAGE

Neurological adverse reactions, including convulsions, may occur with the attainment of high CSF levels of beta-lactams. Ampicillin may be removed from circulation by hemodialysis. The molecular weight, degree of protein binding and pharmacokinetics profile of sulbactam suggest that this compound may also be removed by hemodialysis.

CLINICAL STUDIES

Skin and Skin Structure Infections in Pediatric Patients

Data from a controlled clinical trial conducted in pediatric patients provided evidence supporting the safety and efficacy of UNASYN for the treatment of skin and skin structure infections. Of 99 pediatric patients evaluable for clinical efficacy, 60 patients received a regimen containing intravenous UNASYN, and 39 patients received a regimen containing intravenous cefuroxime. This trial demonstrated similar outcomes (assessed at an appropriate interval after discontinuation of all antimicrobial therapy) for UNASYN- and cefuroxime-treated patients:

TABLE 2
Therapeutic Regimen | Clinical Success | Clinical Failure
UNASYN | 51/60 (85%) | 9/60 (15%)
Cefuroxime | 34/39 (87%) | 5/39 (13%)

Most patients received a course of oral antimicrobials following initial treatment with intravenous administration of parenteral antimicrobials. The study protocol required that the following three criteria be met prior to transition from intravenous to oral antimicrobial therapy: (1) receipt of a minimum of 72 hours of intravenous therapy; (2) no documented fever for prior 24 hours; and (3) improvement or resolution of the signs and symptoms of infection.

The choice of oral antimicrobial agent used in this trial was determined by susceptibility testing of the original pathogen, if isolated, to oral agents available. The course of oral antimicrobial therapy should not routinely exceed 14 days.

DOSAGE AND ADMINISTRATION

UNASYN may be administered by either the IV or the IM routes.

For IV administration, the dose can be given by slow intravenous injection over at least 10–15 minutes or can also be delivered in greater dilutions with 50–100 mL of a compatible diluent as an intravenous infusion over 15–30 minutes.

UNASYN may be administered by deep intramuscular injection. (see DIRECTIONS FOR USE-Preparation for Intramuscular Injection section).

The recommended adult dosage of UNASYN is 1.5 g (1 g ampicillin as the sodium salt plus 0.5 g sulbactam as the sodium salt) to 3 g (2 g ampicillin as the sodium salt plus 1 g sulbactam as the sodium salt) every six hours. This 1.5 to 3 g range represents the total of ampicillin content plus the sulbactam content of UNASYN, and corresponds to a range of 1 g ampicillin plus 0.5 g sulbactam to 2 g ampicillin plus 1 g sulbactam. The total dose of sulbactam should not exceed 4 grams per day.

Pediatric Patients 1 Year of Age or Older

The recommended daily dose of UNASYN in pediatric patients is 300 mg per kg of body weight administered via intravenous infusion in equally divided doses every 6 hours. This 300 mg/kg/day dosage represents the total ampicillin content plus the sulbactam content of UNASYN, and corresponds to 200 mg ampicillin/100 mg sulbactam per kg per day. The safety and efficacy of UNASYN administered via intramuscular injection in pediatric patients have not been established. Pediatric patients weighing 40 kg or more should be dosed according to adult recommendations, and the total dose of sulbactam should not exceed 4 grams per day. The course of intravenous therapy should not routinely exceed 14 days. In clinical trials, most children received a course of oral antimicrobials following initial treatment with intravenous UNASYN. (see CLINICAL STUDIES section).

Impaired Renal Function

In patients with impairment of renal function the elimination kinetics of ampicillin and sulbactam are similarly affected, hence the ratio of one to the other will remain constant whatever the renal function. The dose of UNASYN in such patients should be administered less frequently in accordance with the usual practice for ampicillin and according to the following recommendations:

TABLE 3 UNASYN Dosage Guide for Patients with Renal Impairment
Creatinine Clearance (mL/min/1.73m^2) | Ampicillin and Sulbactam Half-Life (Hours) | Recommended UNASYN Dosage
≥30 | 1 | 1.5–3 g q 6h–q 8h
15–29 | 5 | 1.5–3 g q 12h
5–14 | 9 | 1.5–3 g q 24h

When only serum creatinine is available, the following formula (based on sex, weight, and age of the patient) may be used to convert this value into creatinine clearance. The serum creatinine should represent a steady state of renal function.

 | Males | weight (kg) × (140 − age) 72 × serum creatinine
 | Females | 0.85 × above value

COMPATIBILITY, RECONSTITUTION AND STABILITY

UNASYN sterile powder is to be stored at or below 30°C (86°F) prior to reconstitution.

When concomitant therapy with aminoglycosides is indicated, UNASYN and aminoglycosides should be reconstituted and administered separately, due to the in vitro inactivation of aminoglycosides by any of the aminopenicillins.

DIRECTIONS FOR USE

General Dissolution Procedures

UNASYN sterile powder for intravenous and intramuscular use may be reconstituted with any of the compatible diluents described in this insert. Solutions should be allowed to stand after dissolution to allow any foaming to dissipate in order to permit visual inspection for complete solubilization.

Preparation for Intravenous Use

1.5 g and 3.0 g Bottles: UNASYN sterile powder in piggyback units may be reconstituted directly to the desired concentrations using any of the following parenteral diluents. Reconstitution of UNASYN, at the specified concentrations, with these diluents provide stable solutions for the time periods indicated in the following table: (After the indicated time periods, any unused portions of solutions should be discarded).

TABLE 4
Diluent | Maximum Concentration (mg/mL) UNASYN (Ampicillin/Sulbactam) | Use Periods
Sterile Water for Injection | 45 (30/15) | 8 hrs at 25°C
 | 45 (30/15) | 48 hrs at 4°C
 | 30 (20/10) | 72 hrs at 4°C
0.9% Sodium Chloride Injection | 45 (30/15) | 8 hrs at 25°C
 | 45 (30/15) | 48 hrs at 4°C
 | 30 (20/10) | 72 hrs at 4°C
5% Dextrose Injection | 30 (20/10) | 2 hrs at 25°C
 | 30 (20/10) | 4 hrs at 4°C
 | 3 (2/1) | 4 hrs at 25°C
Lactated Ringer's Injection | 45 (30/15) | 8 hrs at 25°C
 | 45 (30/15) | 24 hrs at 4°C
M/6 Sodium Lactate Injection | 45 (30/15) | 8 hrs at 25°C
 | 45 (30/15) | 8 hrs at 4°C
5% Dextrose in 0.45% Saline | 3 (2/1) | 4 hrs at 25°C
 | 15 (10/5) | 4 hrs at 4°C
10% Invert Sugar | 3 (2/1) | 4 hrs at 25°C
 | 30 (20/10) | 3 hrs at 4°C

If piggyback bottles are unavailable, standard vials of UNASYN sterile powder may be used. Initially, the vials may be reconstituted with Sterile Water for Injection to yield solutions containing 375 mg UNASYN per mL (250 mg ampicillin plus 125 mg sulbactam per mL). An appropriate volume should then be immediately diluted with a suitable parenteral diluent to yield solutions containing 3 to 45 mg UNASYN per mL (2 to 30 mg ampicillin plus 1 to 15 mg sulbactam per mL).

Preparation for Intramuscular Injection

1.5 g and 3.0 g Standard Vials

Vials for intramuscular use may be reconstituted with Sterile Water for Injection USP, 0.5% Lidocaine Hydrochloride Injection USP or 2% Lidocaine Hydrochloride Injection USP. Consult the following table for recommended volumes to be added to obtain solutions containing 375 mg UNASYN per mL (250 mg ampicillin plus 125 mg sulbactam per mL). Note: Use only freshly prepared solutions and administer within one hour after preparation.

TABLE 6
UNASYN Vial Size | Volume of Diluent to be Added | Withdrawal Volume [There is sufficient excess present to allow withdrawal and administration of the stated volumes.]
1.5 g | 3.2 mL | 4.0 mL
3.0 g | 6.4 mL | 8.0 mL

Animal Pharmacology

While reversible glycogenosis was observed in laboratory animals, this phenomenon was dose- and time-dependent and is not expected to develop at the therapeutic doses and corresponding plasma levels attained during the relatively short periods of combined ampicillin sodium and sulbactam sodium therapy in man.

HOW SUPPLIED

UNASYN® (ampicillin sodium and sulbactam sodium) for Injection, USP is supplied as a sterile off-white dry powder in glass vials and piggyback bottles. The following packages are available:

Vials containing 1.5 g (NDC 0049-0013-83) equivalent of UNASYN (1 g ampicillin as the sodium salt plus 0.5 g sulbactam as the sodium salt).

Vials containing 3 g (NDC 0049-0014-83) equivalent of UNASYN (2 g ampicillin as the sodium salt plus 1 g sulbactam as the sodium salt).

To report SUSPECTED ADVERSE EVENTS, contact Pfizer Inc. at 1-800-438-1985 or FDA at 1-800-FDA-1088 or http://www.fda.gov/ for voluntary reporting of adverse reactions.

This product's labeling may have been updated. For the most recent prescribing information, please visit www.pfizer.com.

For medical information about UNASYN, please visit www.pfizermedicalinformation.com or call 1-800-438-1985.

LAB-0017-26.0
Revised April 2025

PRINCIPAL DISPLAY PANEL - 1.5 g Vial Label

NDC 0049-0013-81
Rx only

Unasyn®

(ampicillin sodium/sulbactam
sodium) for Injection

1.5 g* per vial

Sterile
For Intramuscular or
Intravenous use

PRINCIPAL DISPLAY PANEL – 1.5 g Vial Carton

NDC 0049-0013-83
contains 10 of NDC 0049-0013-81

Rx only

10 Vials

Unasyn®
(ampicillin sodium/sulbactam sodium)
for Injection

1.5 g* per vial

Sterile
For Intramuscular or Intravenous use

Pfizer

PRINCIPAL DISPLAY PANEL - 3 g Vial Label

NDC 0049-0014-81
Rx only

Unasyn®
(ampicillin sodium/
sulbactam sodium)
for Injection

3 g* per vial

Sterile
For Intramuscular or
Intravenous use

PRINCIPAL DISPLAY PANEL – 3 g Vial Carton

NDC 0049-0014-83
contains 10 of NDC 0049-0014-81
Rx only

10 Vials

Unasyn®
(ampicillin sodium/sulbactam sodium)
for Injection

3 g* per vial

Sterile
For Intramuscular or Intravenous use

Pfizer